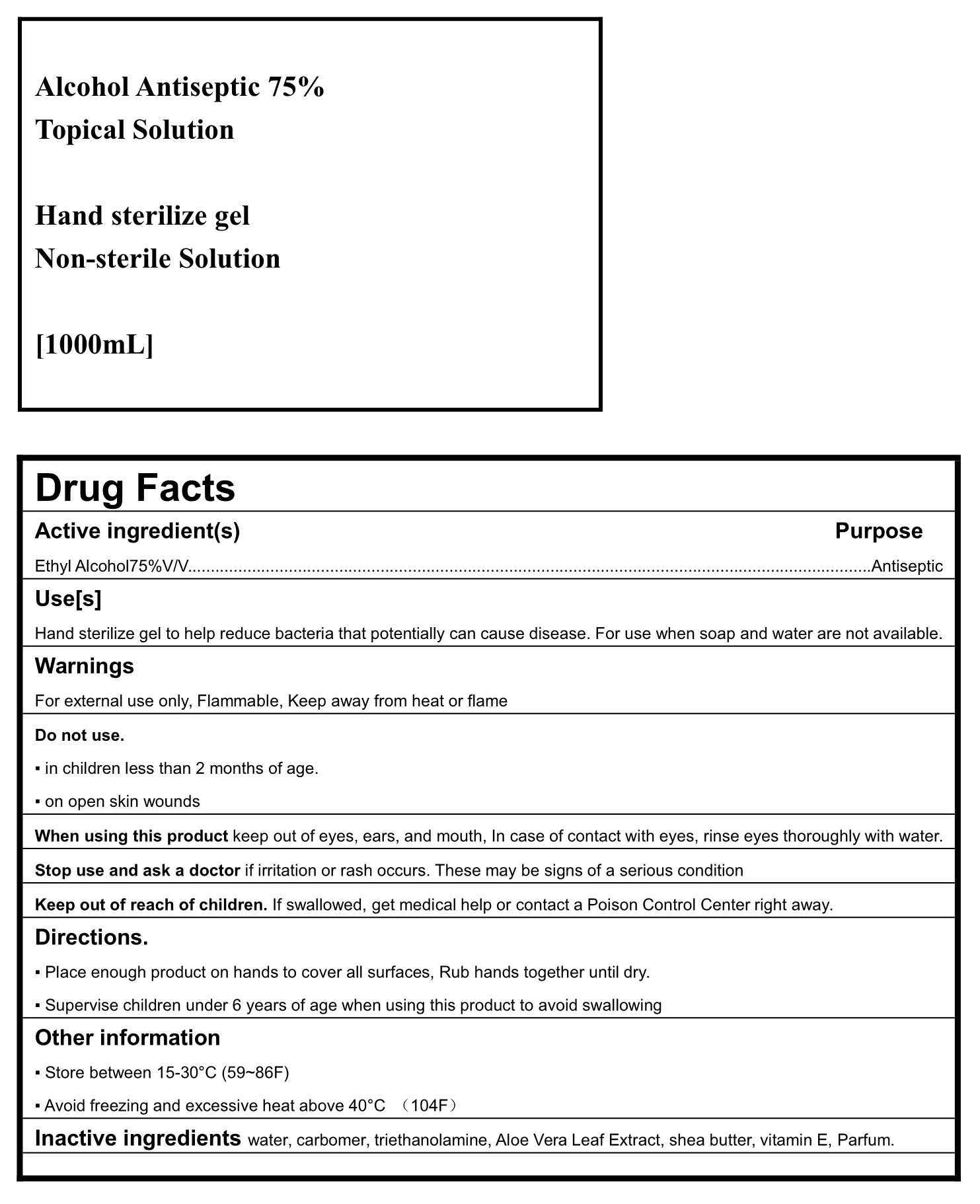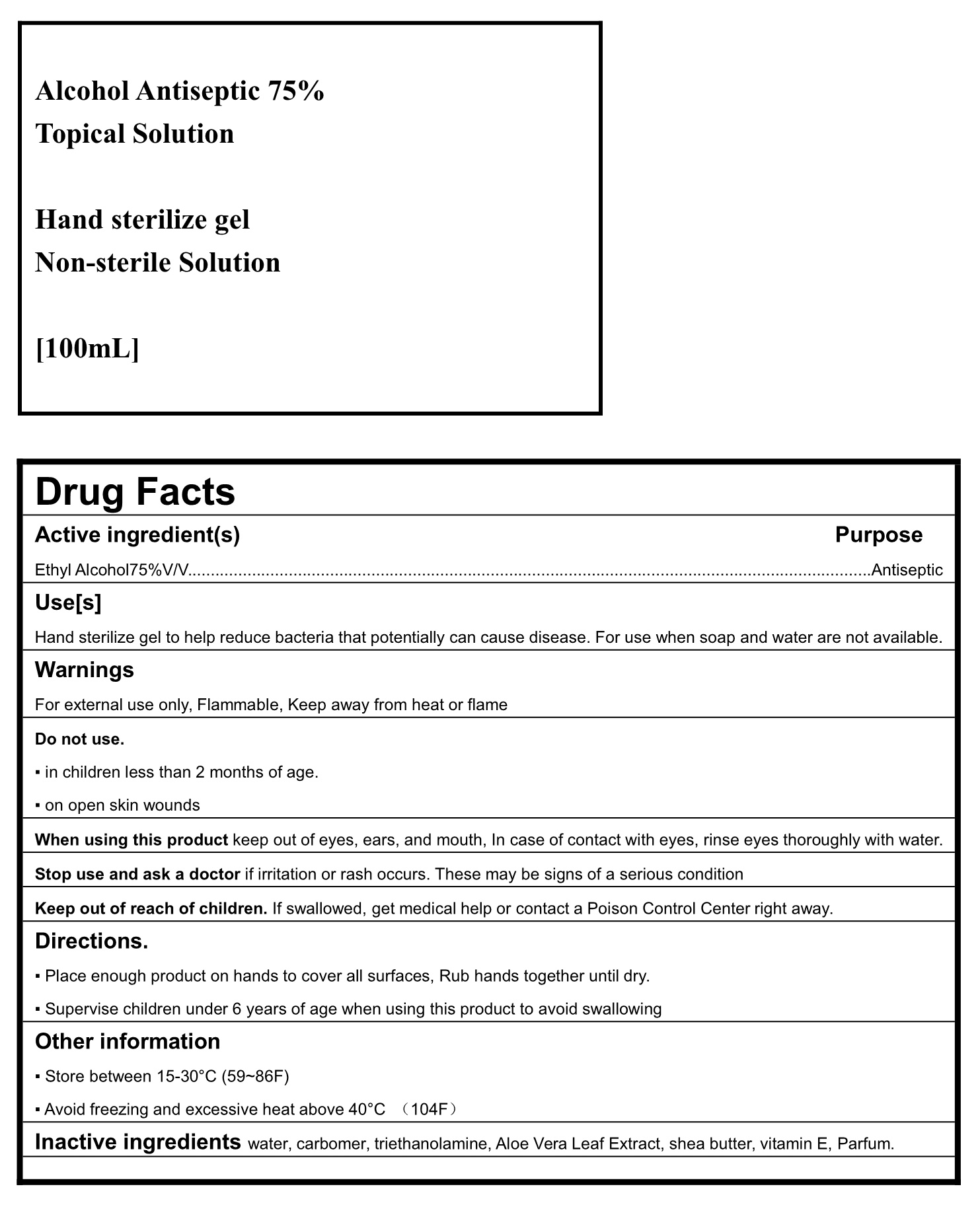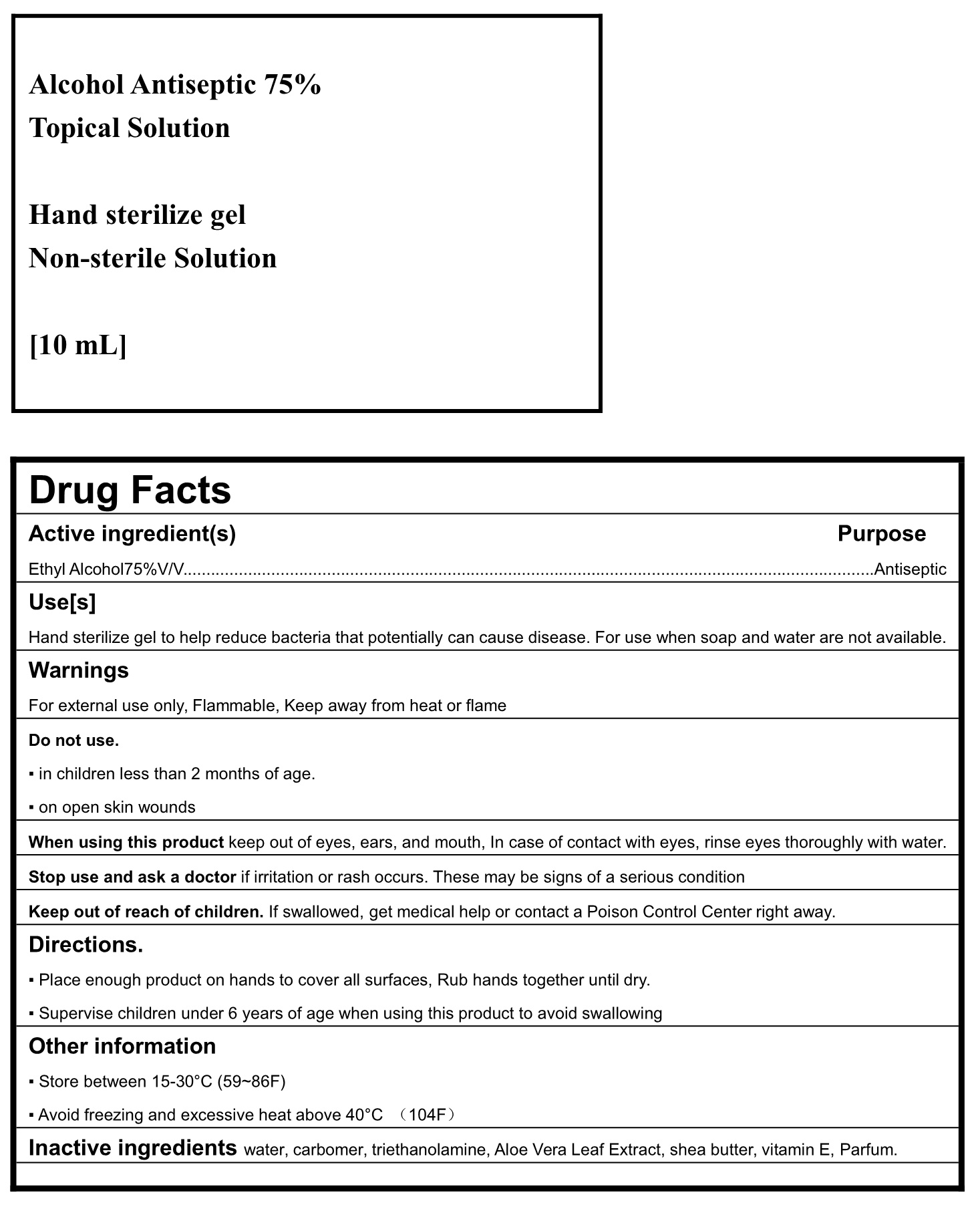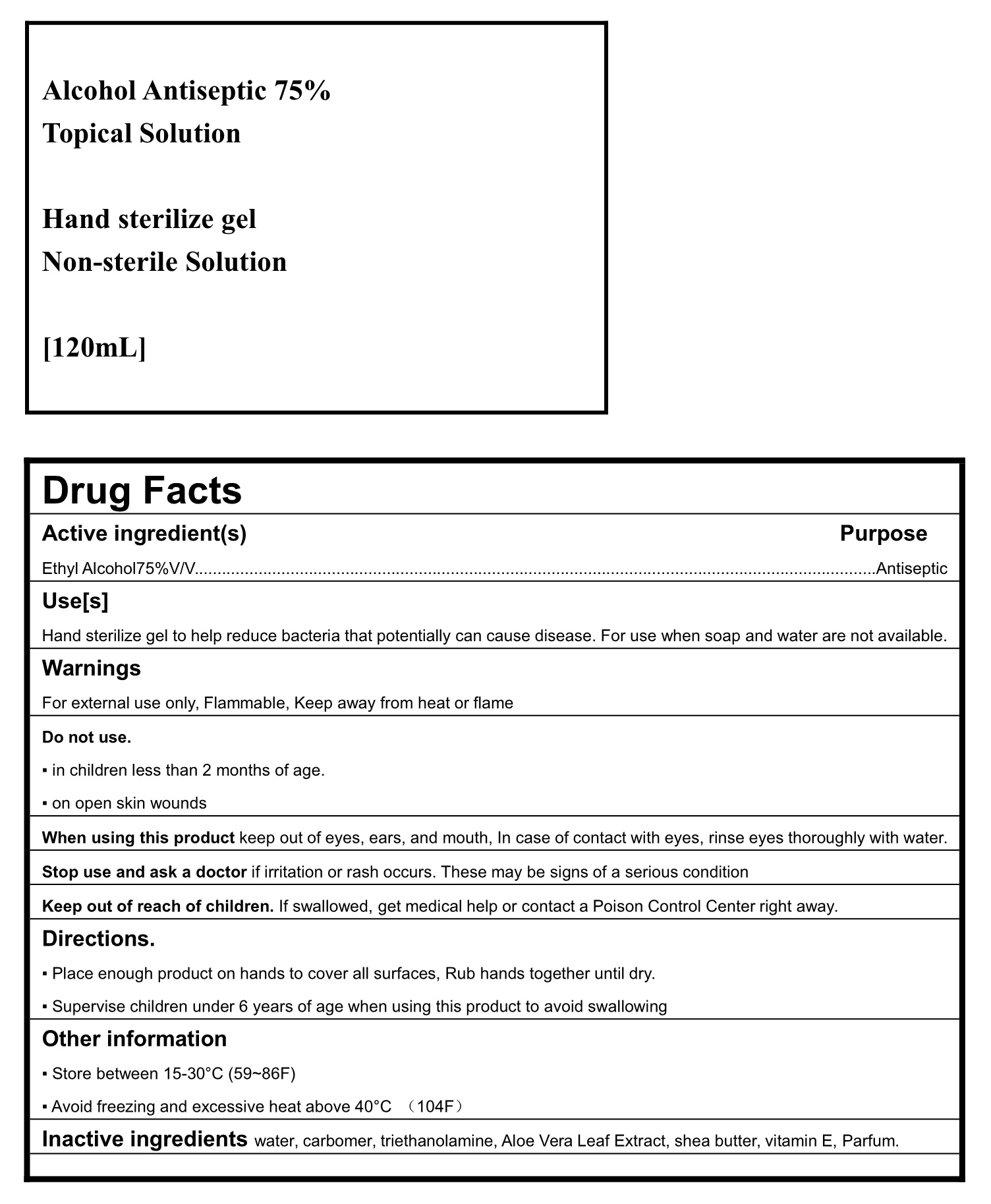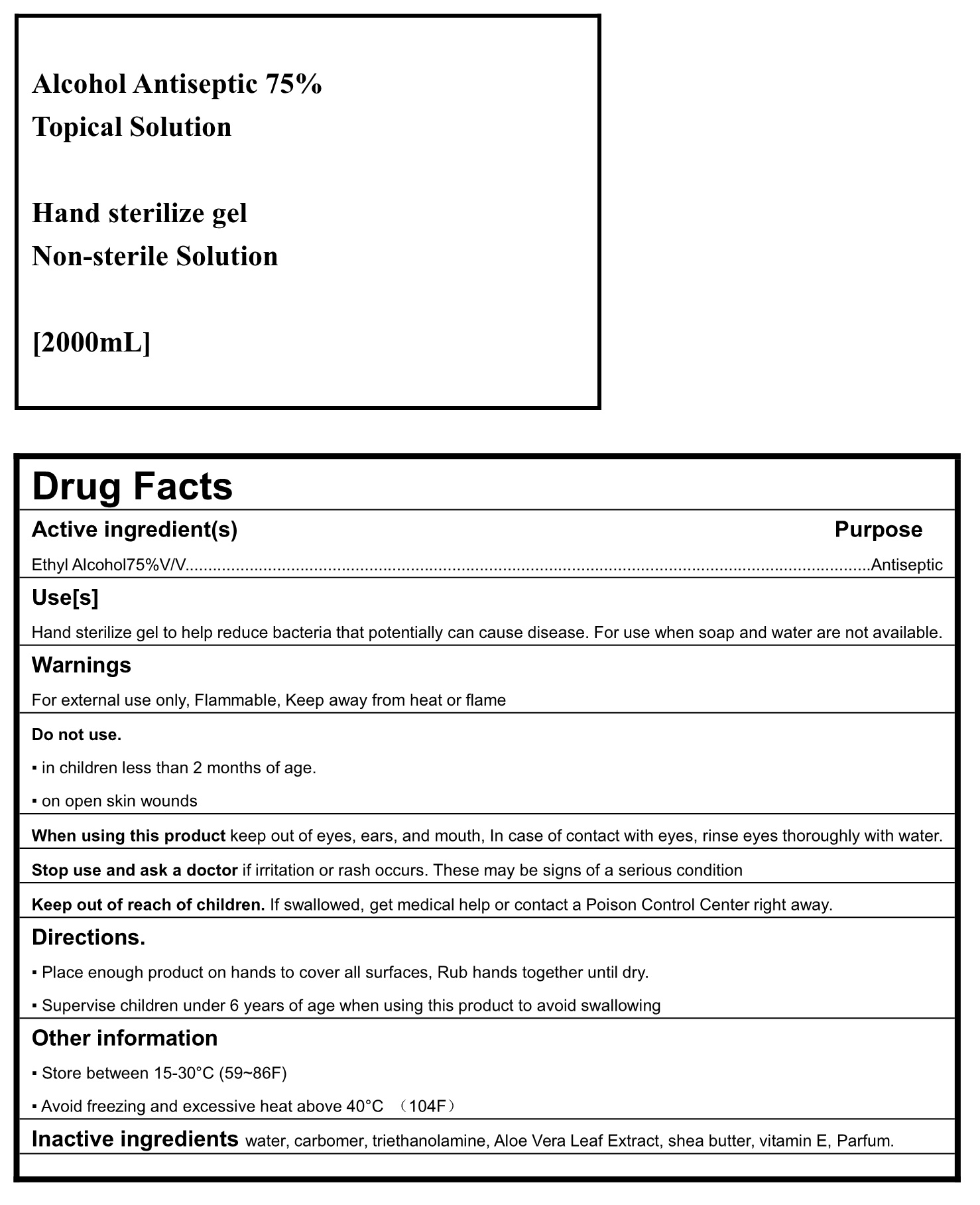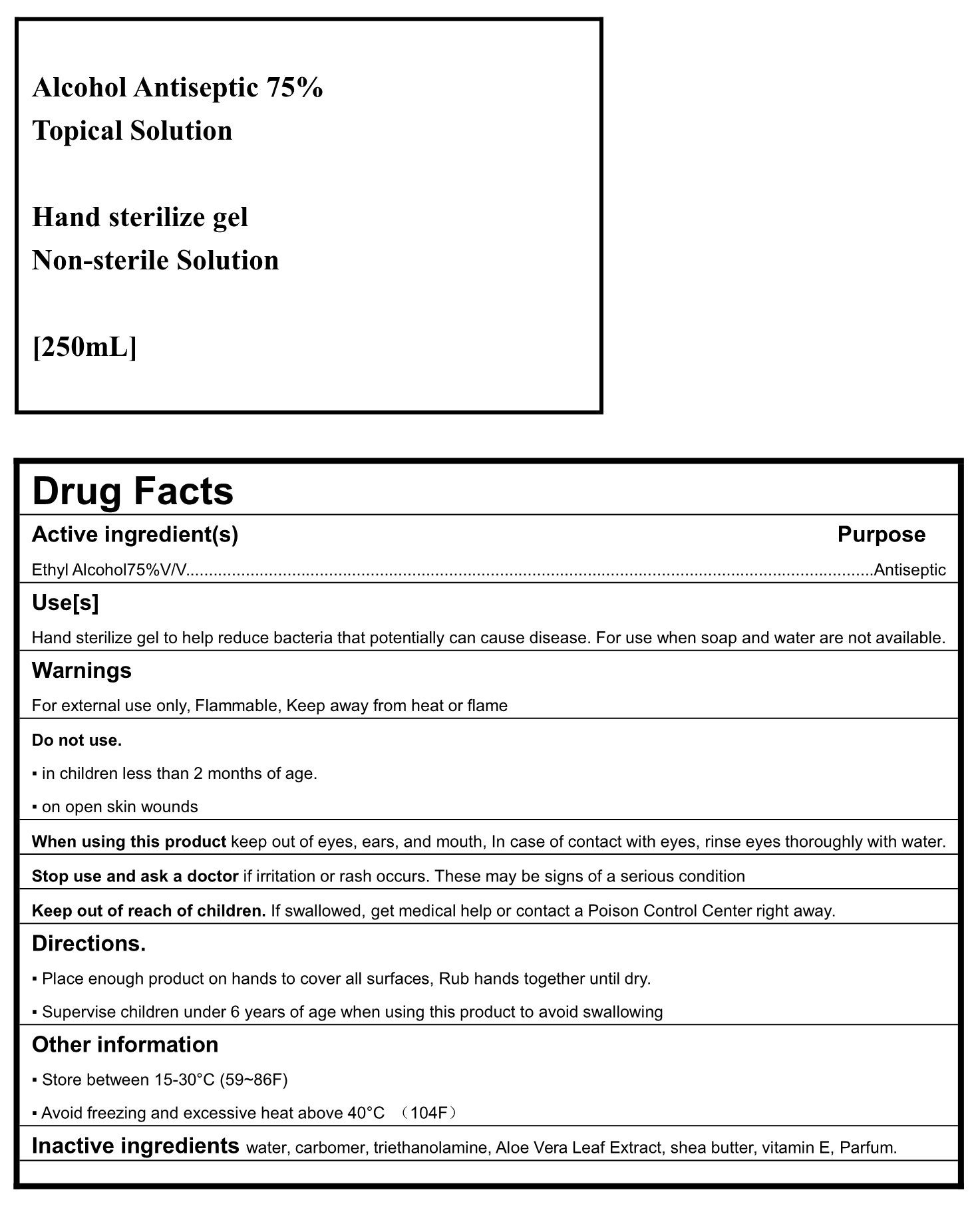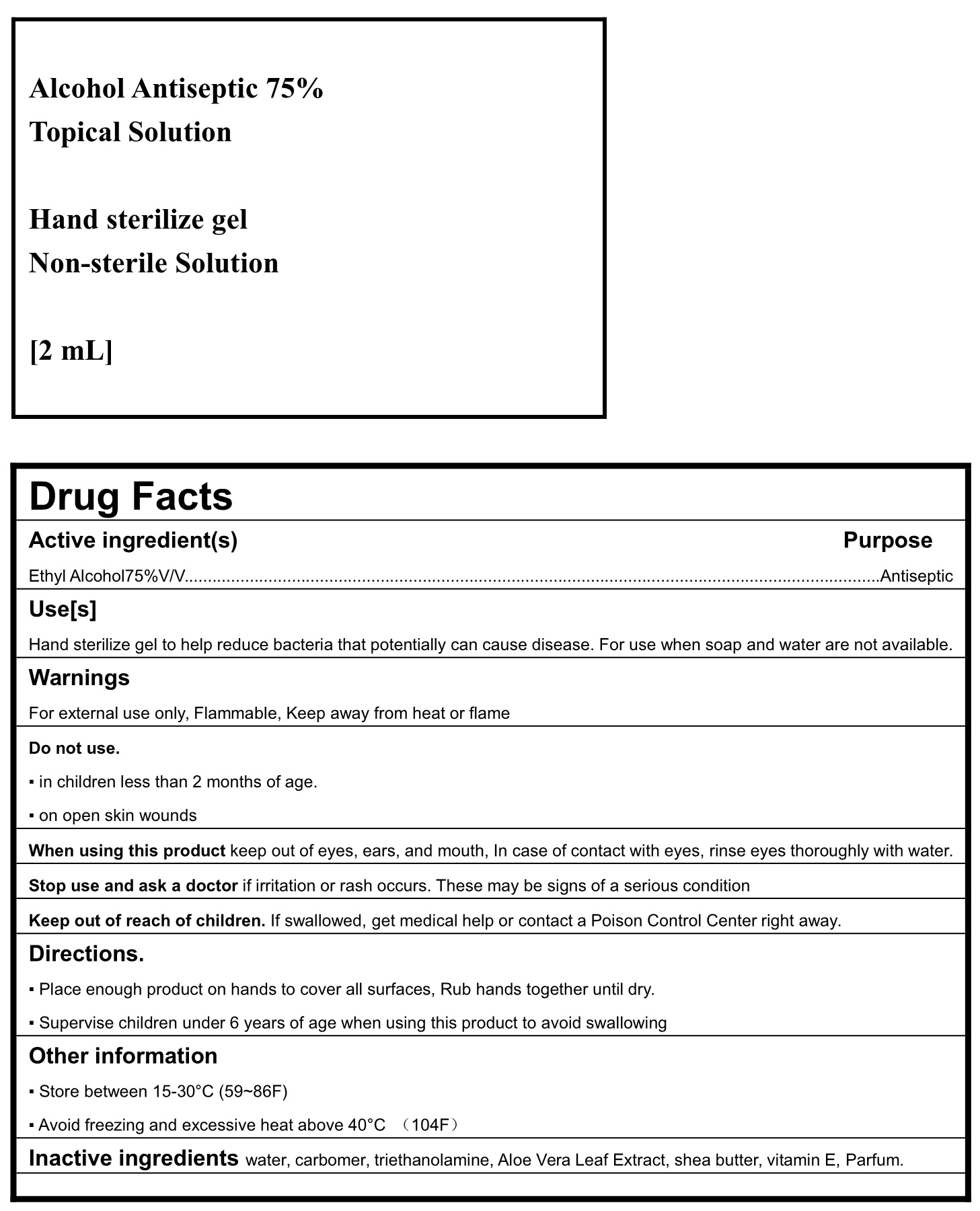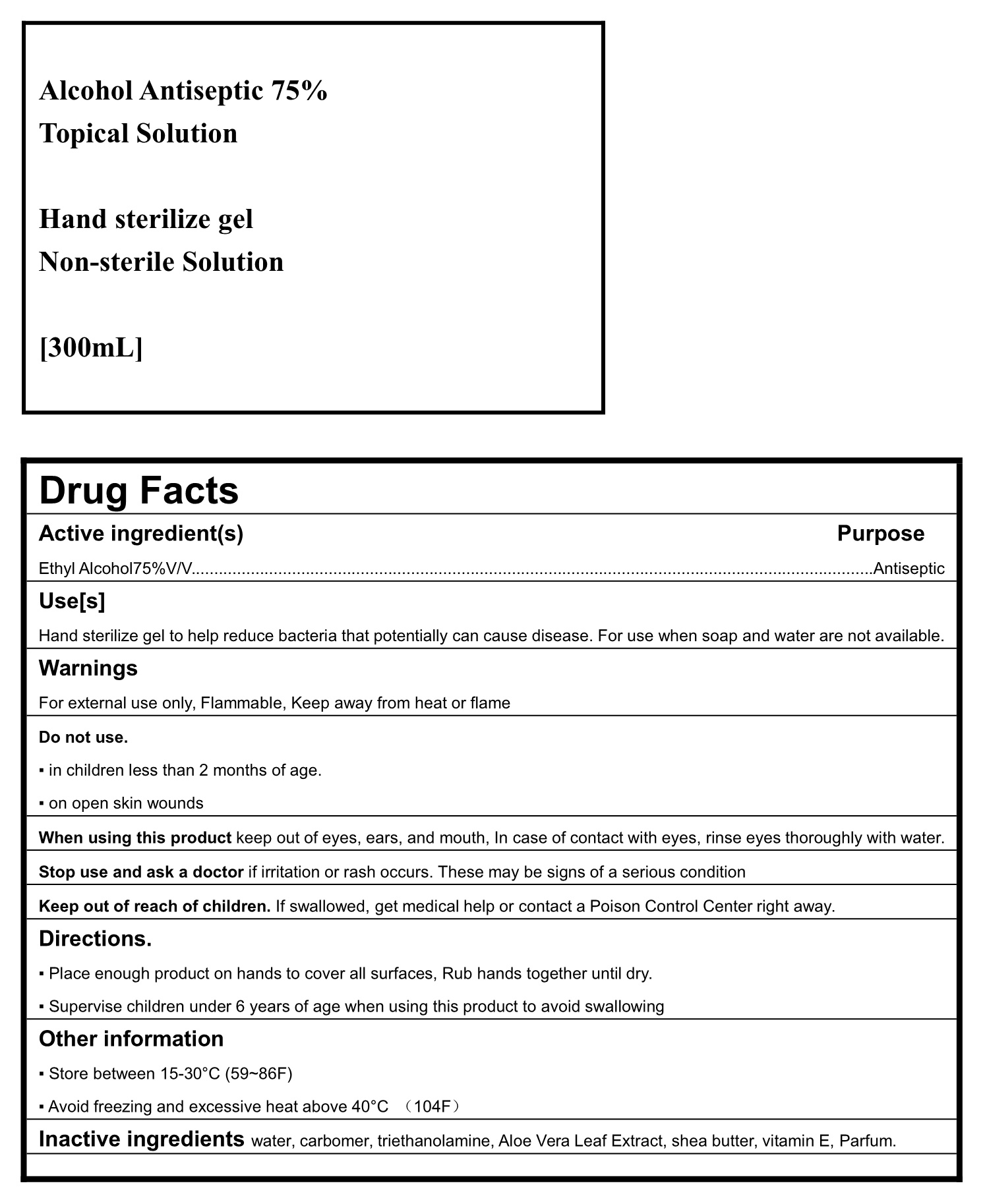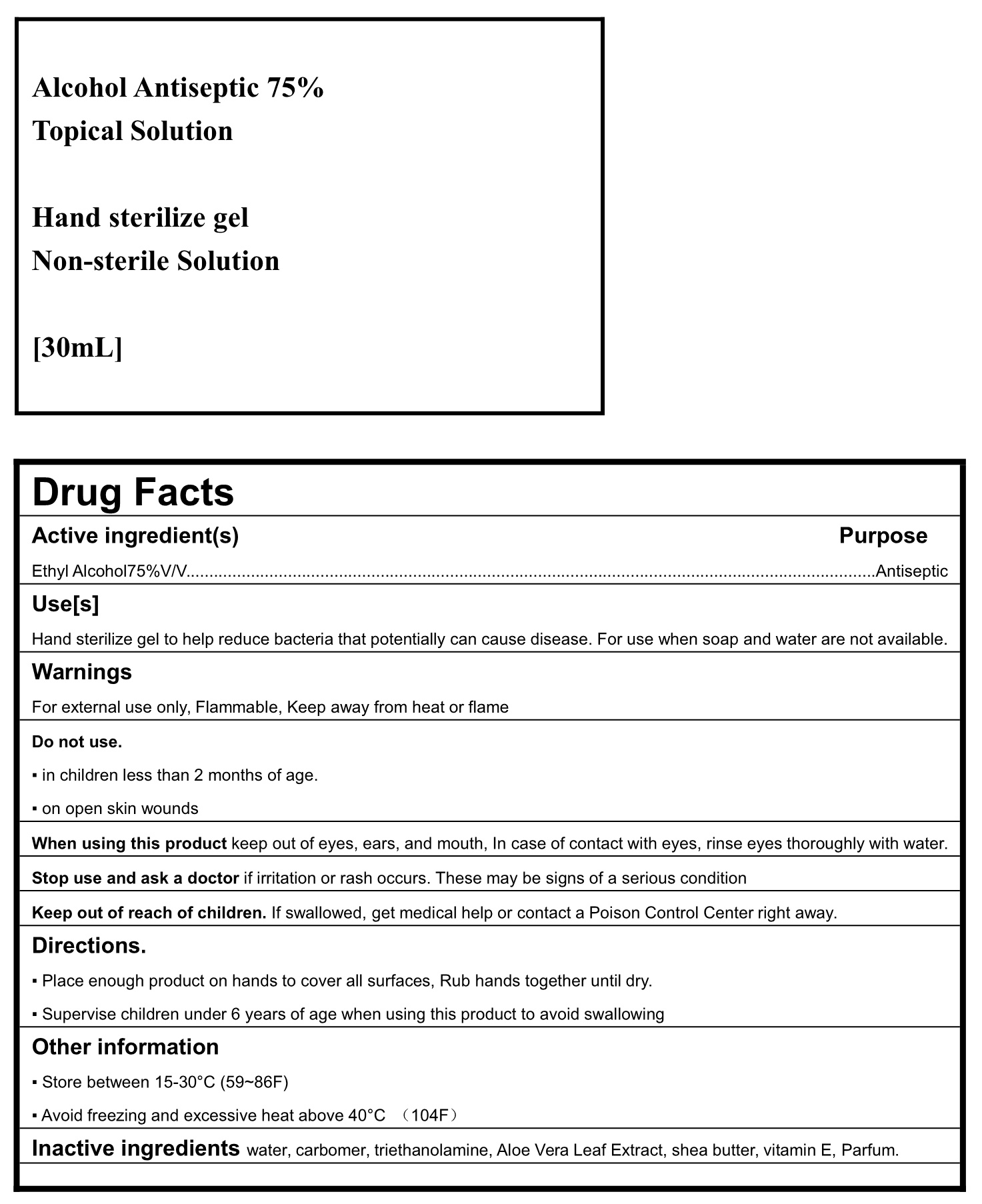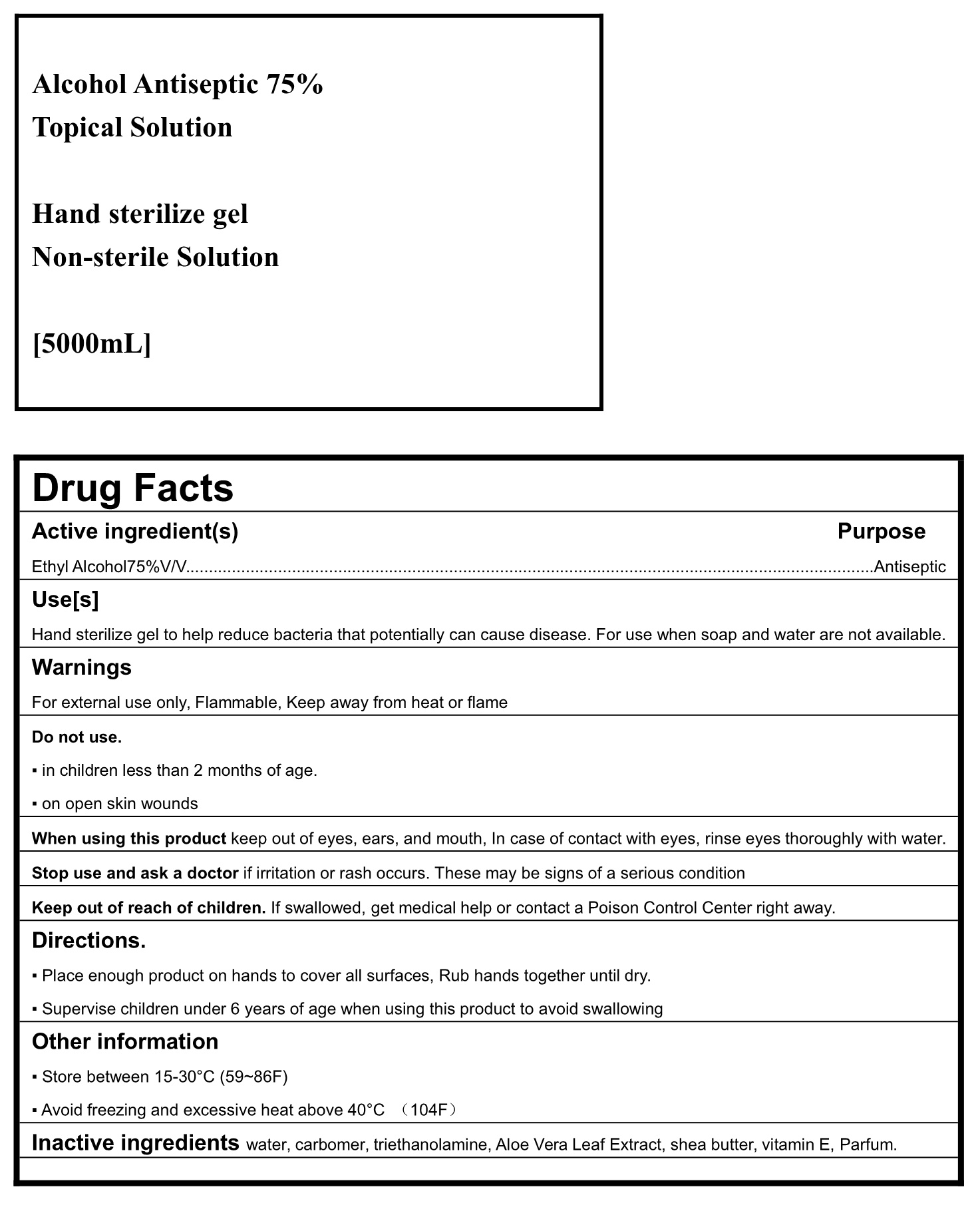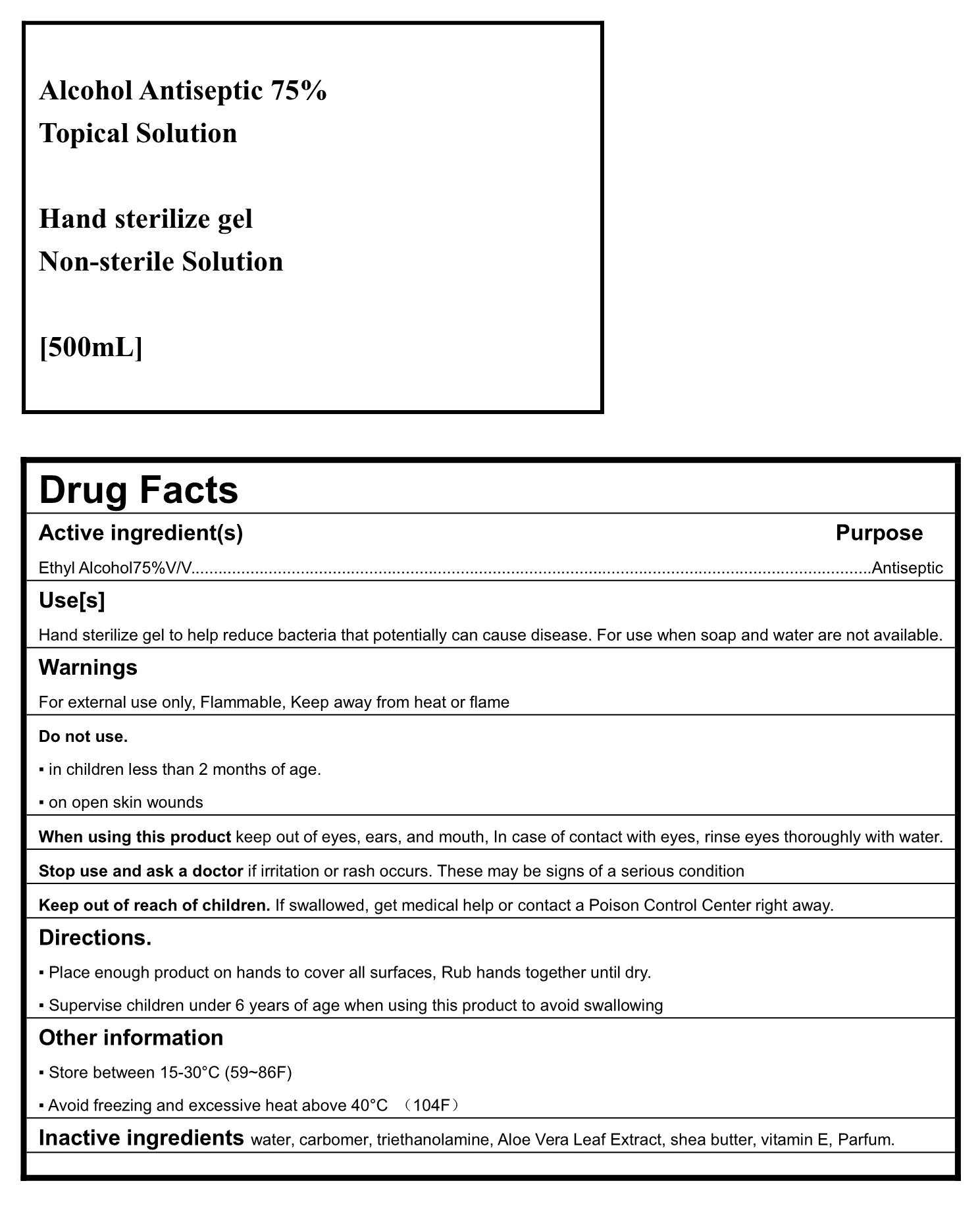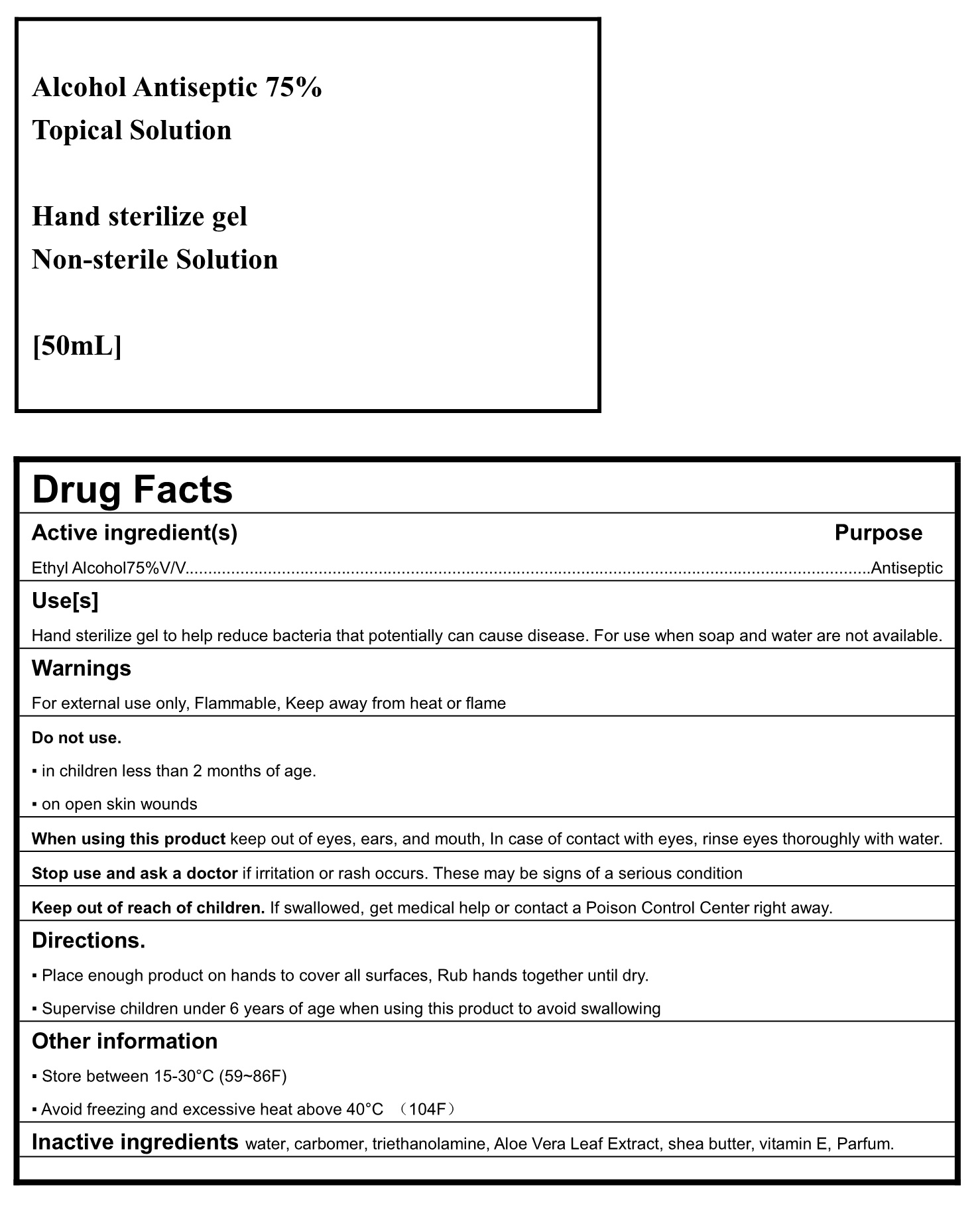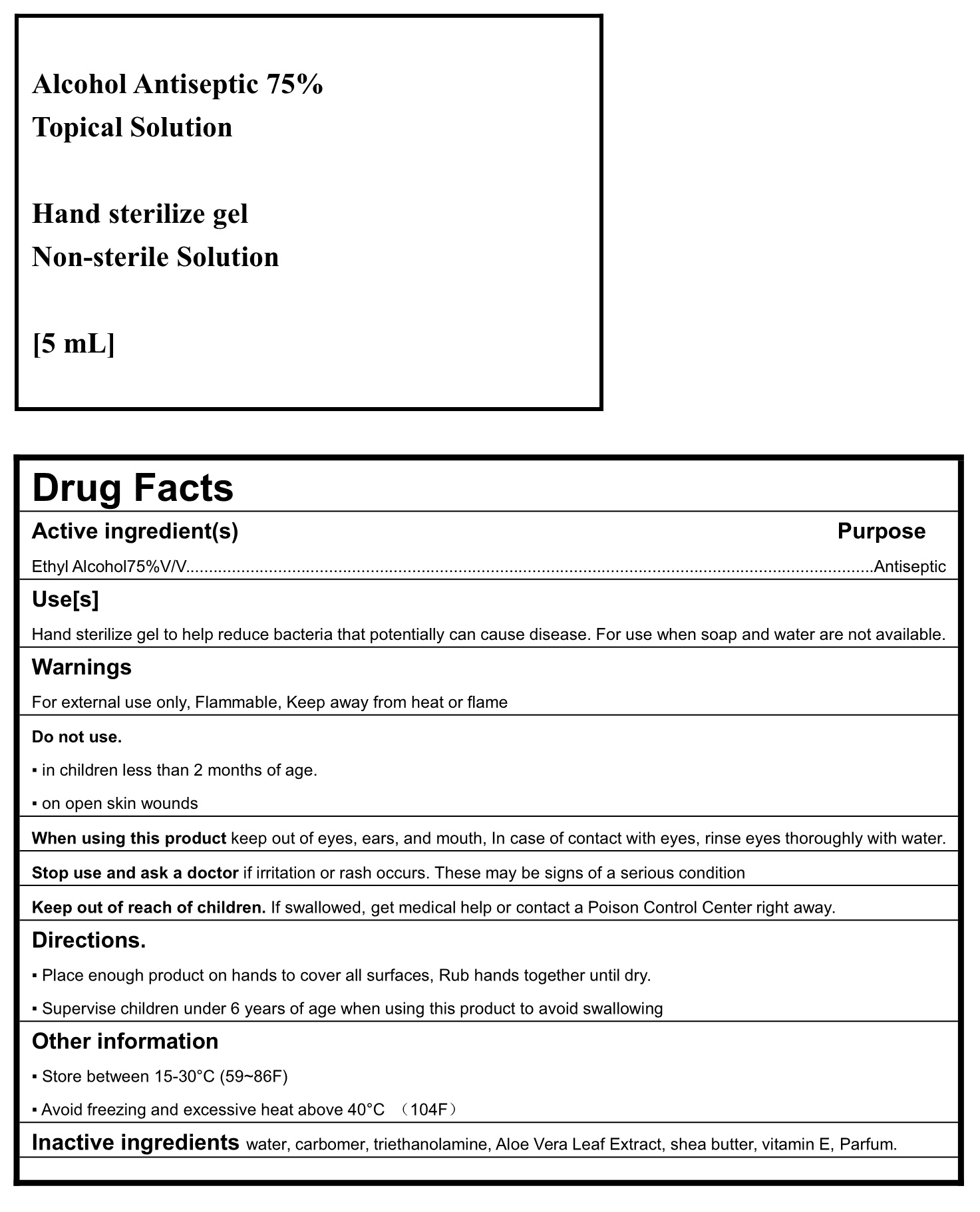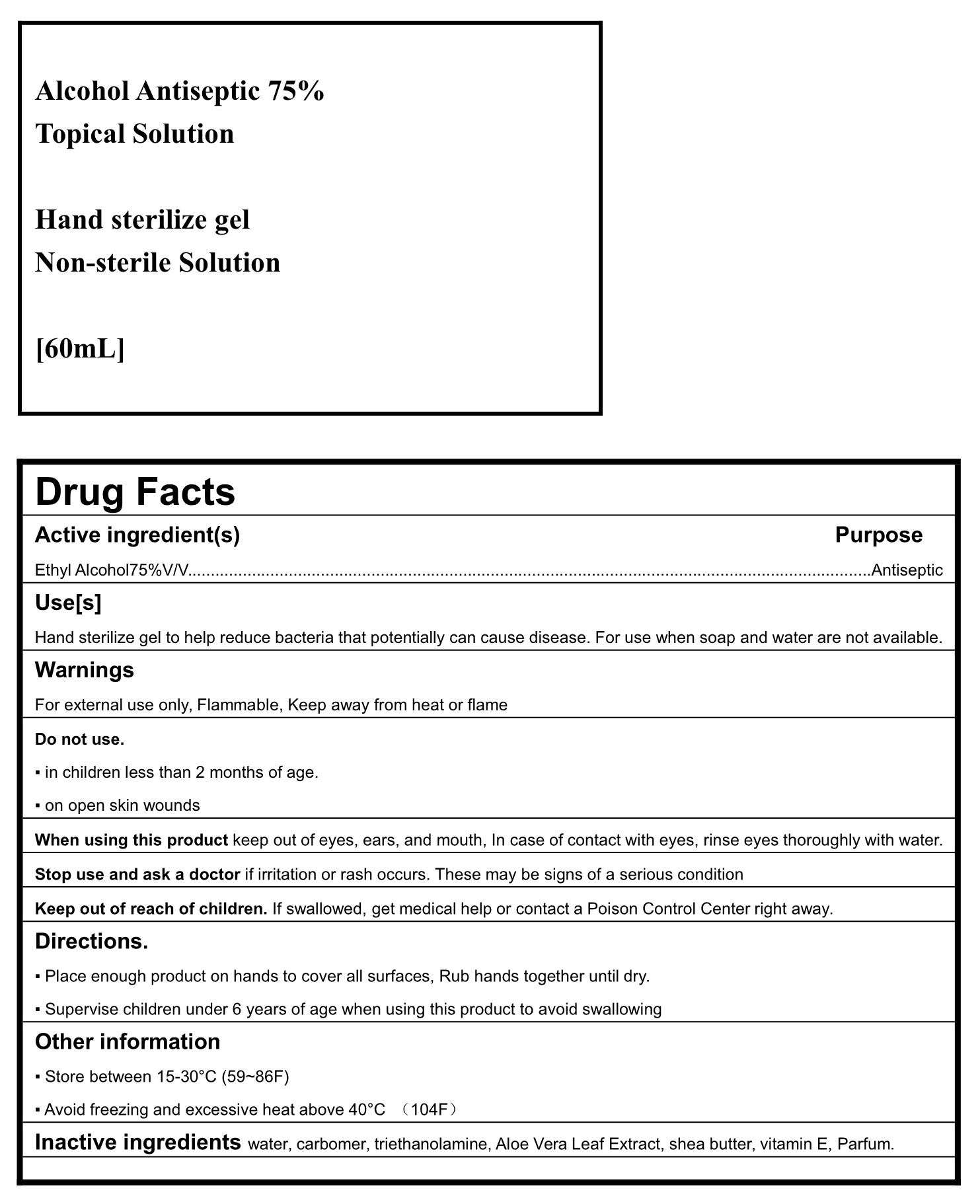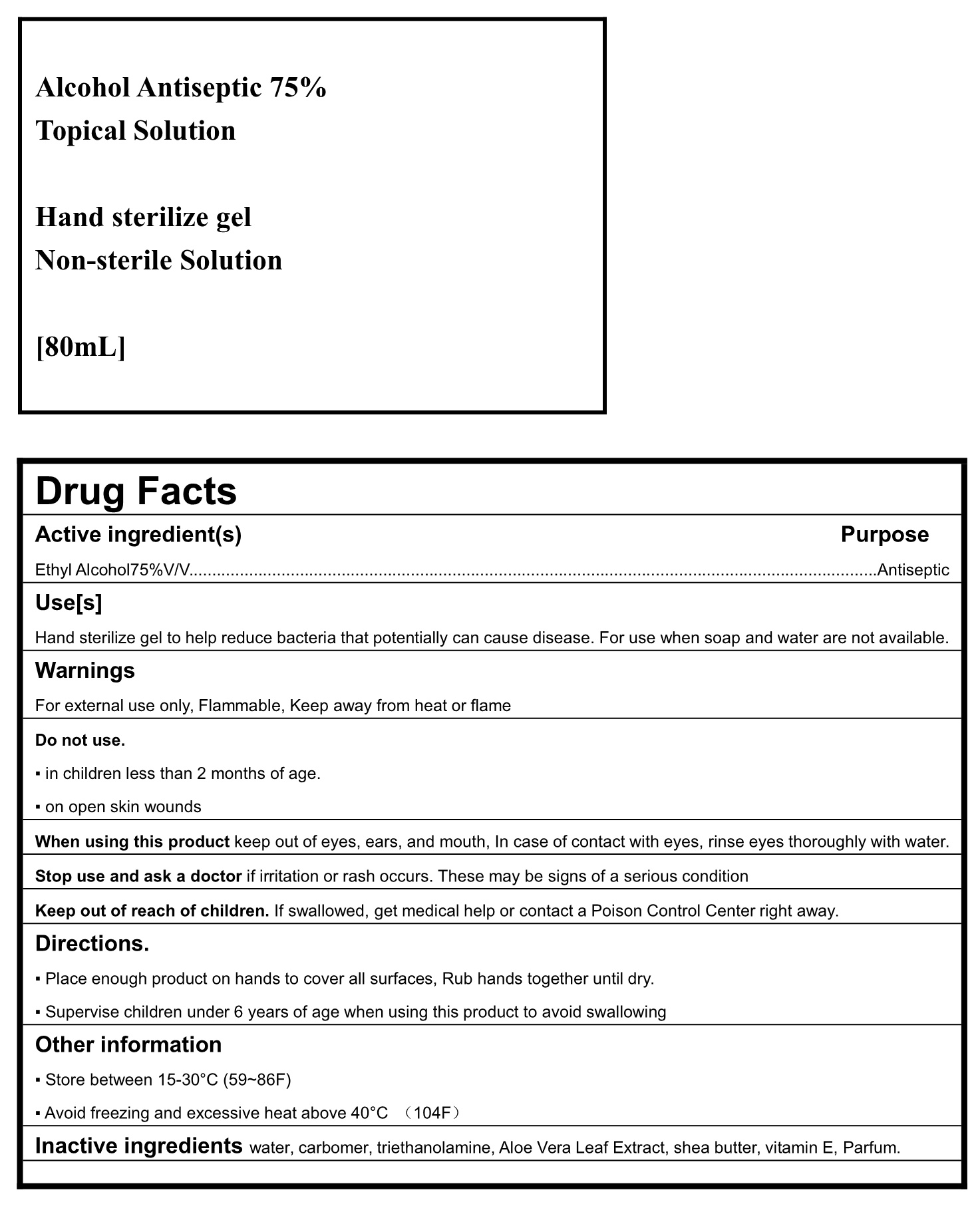 DRUG LABEL: Hand Sanitizer
NDC: 78520-001 | Form: GEL
Manufacturer: Guangzhou Coral Industrial Co., Ltd.
Category: otc | Type: HUMAN OTC DRUG LABEL
Date: 20200612

ACTIVE INGREDIENTS: ALCOHOL 71 mL/100 mL
INACTIVE INGREDIENTS: CARBOMER 980 0.4 mL/100 mL; SHEA BUTTER 0.01 mL/100 mL; WATER 28.37 mL/100 mL

This is a hand sanitizer manufactured according to the Temporary Policy for Preparation of Certain Alcohol-Based Hand Sanitizer Products During the Public Health Emergency (CoViD-19); Guidance for Industry.

The hand sanitizer is manufactured using only the following United States Pharmacopoeia (USP) grade ingredients in the preparation of the product (percentage in final product formulation) consistent with World Health Organization (WHO) recommendations:

1. Isopropyl Alcohol (75%, v/v) in an aqueous solution denatured according to Alcohol and Tobacco Tax and Trade Bureau regulations in 27 CFR part 20.
2. Carbomer (0.4% v/v).
3. Triethanolamine (0.2% v/v).
4. Sterile distilled water or boiled cold water.

The firm does not add other active or inactive ingredients. Different or additional ingredients may impact the quality and potency of the product.

Active Ingredient(s)

Isopropyl Alcohol 75% v/v. Purpose: Antiseptic

Purpose

Antiseptic, Hand Sanitizer

Use

Hand Sanitizer to help reduce bacteria that potentially can cause disease. For use when soap and water are not available.

Warnings

For external use only. Flammable. Keep away from heat or flame

Do not use

- in children less than 2 months of age
- on open skin wounds

When using this product keep out of eyes, ears, and mouth. In case of contact with eyes, rinse eyes thoroughly with water.
Stop use and ask a doctor if irritation or rash occurs. These may be signs of a serious condition.
Keep out of reach of children. If swallowed, get medical help or contact a Poison Control Center right away.

Stop use and ask a doctor if irritation or rash occurs. These may be signs of a serious condition.

Keep out of reach of children. If swallowed, get medical help or contact a Poison Control Center right away.

Directions

- Place enough product on hands to cover all surfaces. Rub hands together until dry.
- Supervise children under 6 years of age when using this product to avoid swallowing.

Other information

- Store between 15-30C (59-86F)
- Avoid freezing and excessive heat above 40C (104F)

Inactive ingredients

water, carbomer, triethanolamine, Aloe Vera Leaf Extract, shea butter, vitamin E, Parfum.

Package Label - Principal Display Panel

2 mL NDC:78520-001-01
5 mL NDC:78520-001-02

10 mL NDC:78520-001-03
30 mL NDC:78520-001-04
50 mL NDC:78520-001-05
60 mL NDC:78520-001-06
80 mL NDC:78520-001-07
100 mL NDC:78520-001-08
120 mL NDC:78520-001-09

250 mL NDC:78520-001-10

300 mL NDC:78520-001-11

500 mL NDC:78520-001-12

1000 mL NDC:78520-001-13

2000 mL NDC:78520-001-14

5000 mL NDC:78520-001-15